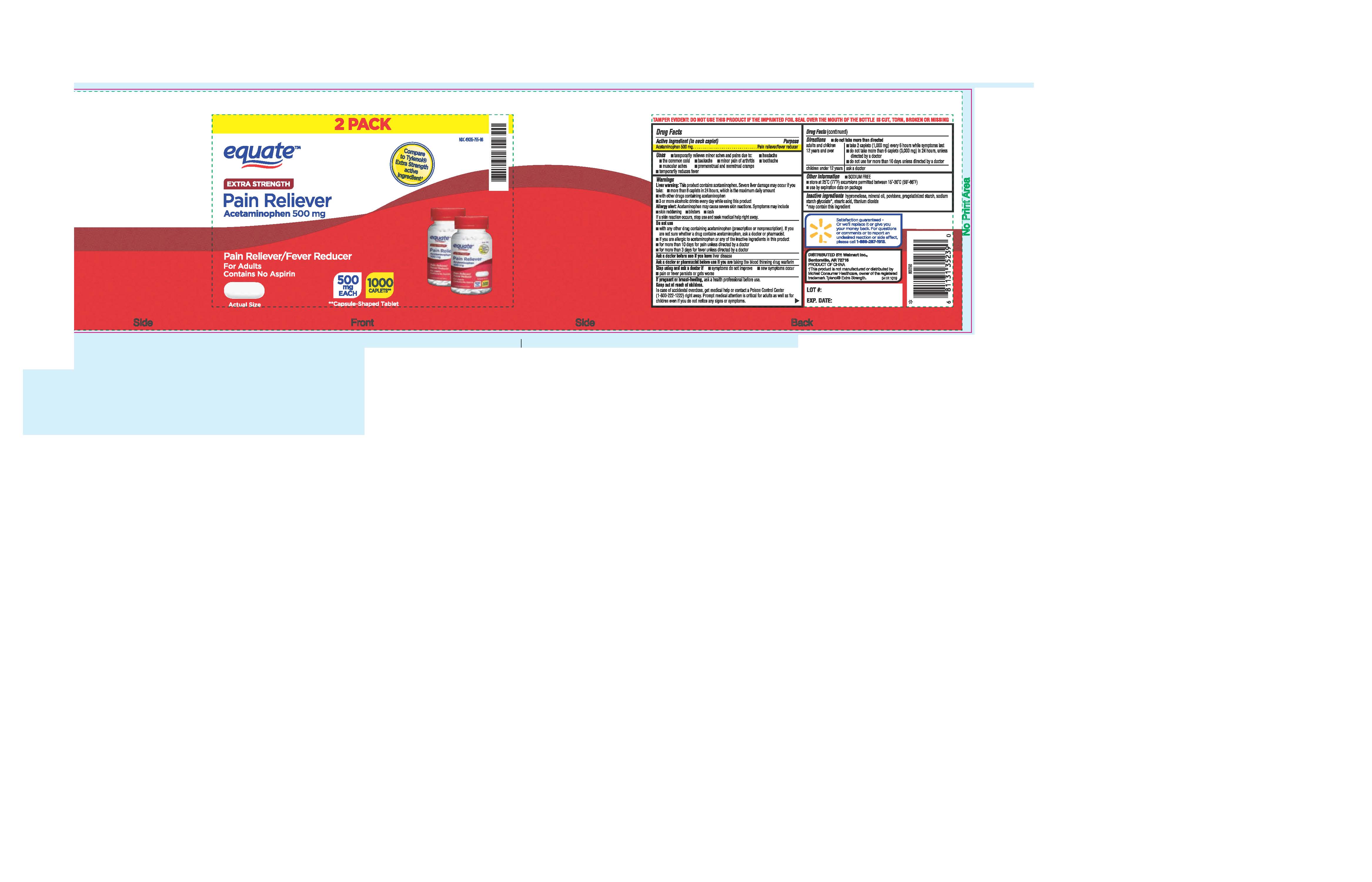 DRUG LABEL: ACETAMINOPHEN
NDC: 49035-755 | Form: TABLET, COATED
Manufacturer: WAL-MART STORES INC
Category: otc | Type: HUMAN OTC DRUG LABEL
Date: 20250111

ACTIVE INGREDIENTS: ACETAMINOPHEN 500 mg/1 1
INACTIVE INGREDIENTS: STEARIC ACID; TITANIUM DIOXIDE; STARCH, CORN; SODIUM STARCH GLYCOLATE TYPE A CORN; HYPROMELLOSES; MINERAL OIL; POVIDONE

341R WALMART APAP 500 MG CAPLETS 49035-755

Active Ingredient (in each caplet)

acetaminophen 500 mg

Purpose

Pain reliever/ fever reducer

INDICATIONS AND USAGE

Uses: - temporarily relieves minor aches and pains due to:

- headache
- the common cold
- backache
- minor pain of arthritis
- toothache
- muscular aches
- premenstrual and menstrual cramps

- temporarily reduces fever

Warnings

Liver warning: This product contains acetaminophen. Severe liver damage may occur if you take:

- more than 8 caplets in 24 hours,which is the maximum daily amount
- with other drugs containing acetaminophen
- 3 or more alcoholic drinks every day while using this product

Allergy alert: acetaminophen may cause severe skin reactions. Symptoms may include:

- skin reddening
- blisters
- rash

If a skin reaction occurs, stop use and seek medical help right away.

Do not use

- with any other drug containing acetaminophen (prescription or nonprescription). If you are not sure whether a drug contains acetaminophen, ask a doctor or pharmacist.
- if you are allergic to acetaminophen or any of the inactive ingredients in this product
- for more than 10 days for pain unless directed by a doctor
- for more than 3 days for fever unless dierected by a doctor

Ask a doctor before use if you have liver disease

Ask a doctor or pharmacist before use if you are taking the blood thinning drug warfarin

Stop using and ask a doctor if

- symptoms do not improve
- new symptoms occur
- pain or fever persists or gets worse

PREGNANCY OR BREAST FEEDING

If pregnant or breast-feeding, ask a health professional before use.

Keep out of reach of children.

In case of accidental overdose, get medical help or contact a Poison Control Center (1-800-222-1222) right away. Prompt medical attention is critical for adults as well as for children even if you do not notice any signs or symptoms.

Directions

- do not take more than directed

adults and children 12 years and over

- take 2 caplets(1,000 mg) every 6 hours while symptoms last
- do not take more than 6 caplets(3,000 mg) in 24 hours, unless directed by a doctor
- do not take for more than 10 days unless directed by a doctor

children under 12 years: ask a doctor

Other information

- SODIUM FREE
- store at 25^0C (77^0F) excursions permitted between 15^0-30^0C (59^0-86^0F)
- use by expiration date on package

INACTIVE INGREDIENT

Inactive ingredients: hypromellose, mineral oil, povidone, pregelatinized starch, sodium starch glycolate*, stearic acid, titanium dioxide
*may contain this ingredient